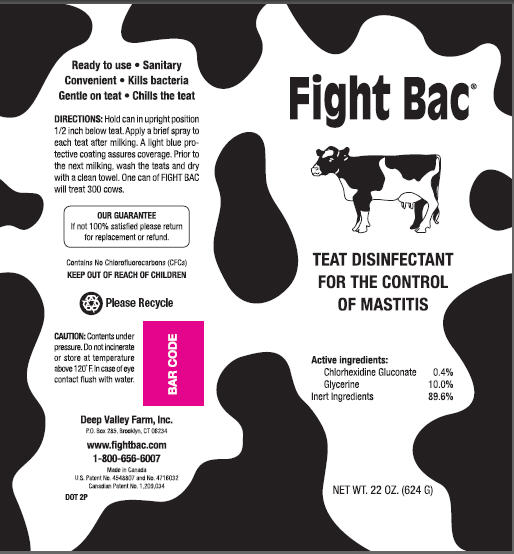 DRUG LABEL: Fight Bac
								
NDC: 49845-001 | Form: AEROSOL
Manufacturer: Deep Valley Farm, Inc.
Category: animal | Type: OTC ANIMAL DRUG LABEL
Date: 20090811

ACTIVE INGREDIENTS: CHLORHEXIDINE GLUCONATE 2 g/ 437 g

FIGHT BAC

- Ready to use
- Sanitary
- Convenient
- Kills bacteria
- Gentle on teat
- Chills the teat

Directions

Hold can in upright position 1/2 below teat. Apply a brief spray to each teat after milking. A light blue protective coating assures coverage. Prior to the next milking, wash the teats and dry with a clean towel. One can of FIGHT BAC will treat 300 cows.

OUR GUARANTEE

If not 100% satisfied please return for replacement or refund.

Contains No Chlorofluorcarbons (CFCs)

KEEP OUT OF REACH OF CHILDREN

Enter section text here

Please Recycle

Caution:

Contents under pressure. Do not incinerate or store at temperature above 120 F. In case of eye contact flush with water.

Deep Valley Farm, Inc.

P.O. Box 285, Brooklyn, CT 06234

www.fightbac.com

1-800-656-6007

Made in Canada

U.S. Patent No. 4548807 and No. 4716032

Canadian Patent No. 1,209,034

DOT 2P

PACKAGE LABEL

Fight Bac

TEAT DISINFECTANT

FOR THE CONTROL

OF MASTITIS

Active ingredients:

Chlorhexidine Gluconate 0.4%

Glycerine 10.0%

Inert Ingredients 89.6%

NET WT. 22 OZ (624 G)